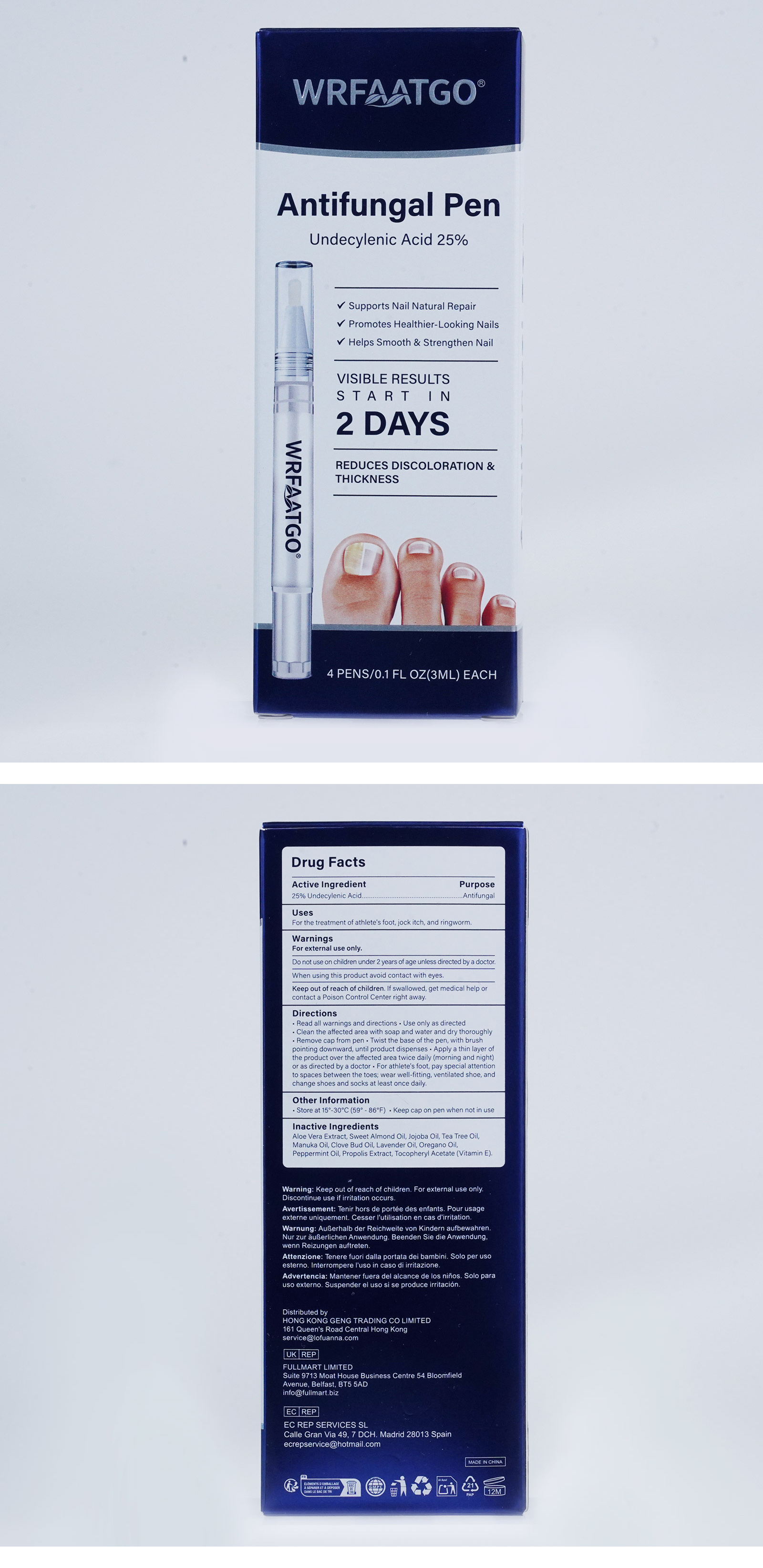 DRUG LABEL: WRFAATGO ANTIFUNGAL Pen Undecylenic Acid 25%
NDC: 83804-012 | Form: LIQUID
Manufacturer: Shenzhen Shandian Jingling Technology Co., Ltd.
Category: otc | Type: HUMAN OTC DRUG LABEL
Date: 20251209

ACTIVE INGREDIENTS: UNDECYLENIC ACID 0.25 g/1 mL
INACTIVE INGREDIENTS: ALMOND OIL; TEA TREE OIL; CLOVE OIL; ALOE VERA LEAF; MANUKA OIL; LAVENDER OIL; .ALPHA.-TOCOPHEROL ACETATE; PEPPERMINT OIL; PROPOLIS WAX; JOJOBA OIL; OREGANO LEAF OIL

83804-012 WRFAATGO ANTIFUNGAL Pen Undecylenic Acid 25%

ACTIVE INGREDIENT

UNDECYLENIC ACID 25%

PURPOSE

Antifungal

INDICATIONS AND USAGE

For the treatment of athlete's foot, jock itch, and ringworm.

WARNINGS

For external use only.

Do not use on children under 2 years of age unless directed by a doctor.

When using this product avoid contact with eyes

STOP USE

If you experience discomfort or allergic reactions during use, please stop using.

Keep out of reach of children, if swallowed, get medical help or contact a Poison Control Center right away.

DOSAGE AND ADMINISTRATION

Read all warnings and directions . Use only as directed.
Clean the affected area with soap and water and dry thoroughly.
Remove cap from pen . Twist the base of the pen, with brush pointing downward, until product dispenses · Apply a thin layer of the product over the affected area twice daily (morning and night) or as directed by a doctor . For athlete's foot, pay special attention to spaces between the toes; wear well-fitting, ventilated shoe, and change shoes and socks at least once daily.

INACTIVE INGREDIENT

ALOE VERA LEAF
SWEET ALMOND OIL
JOJOBA OIL
TEA TREE OIL
MANUKA OIL
CLOVE BUD OIL
LAVENDER OIL
OREGANO OIL
PEPPERMINT OIL
PROPOLIS WAX
ALPHA.-TOCOPHEROL ACETATE (vitamin E)